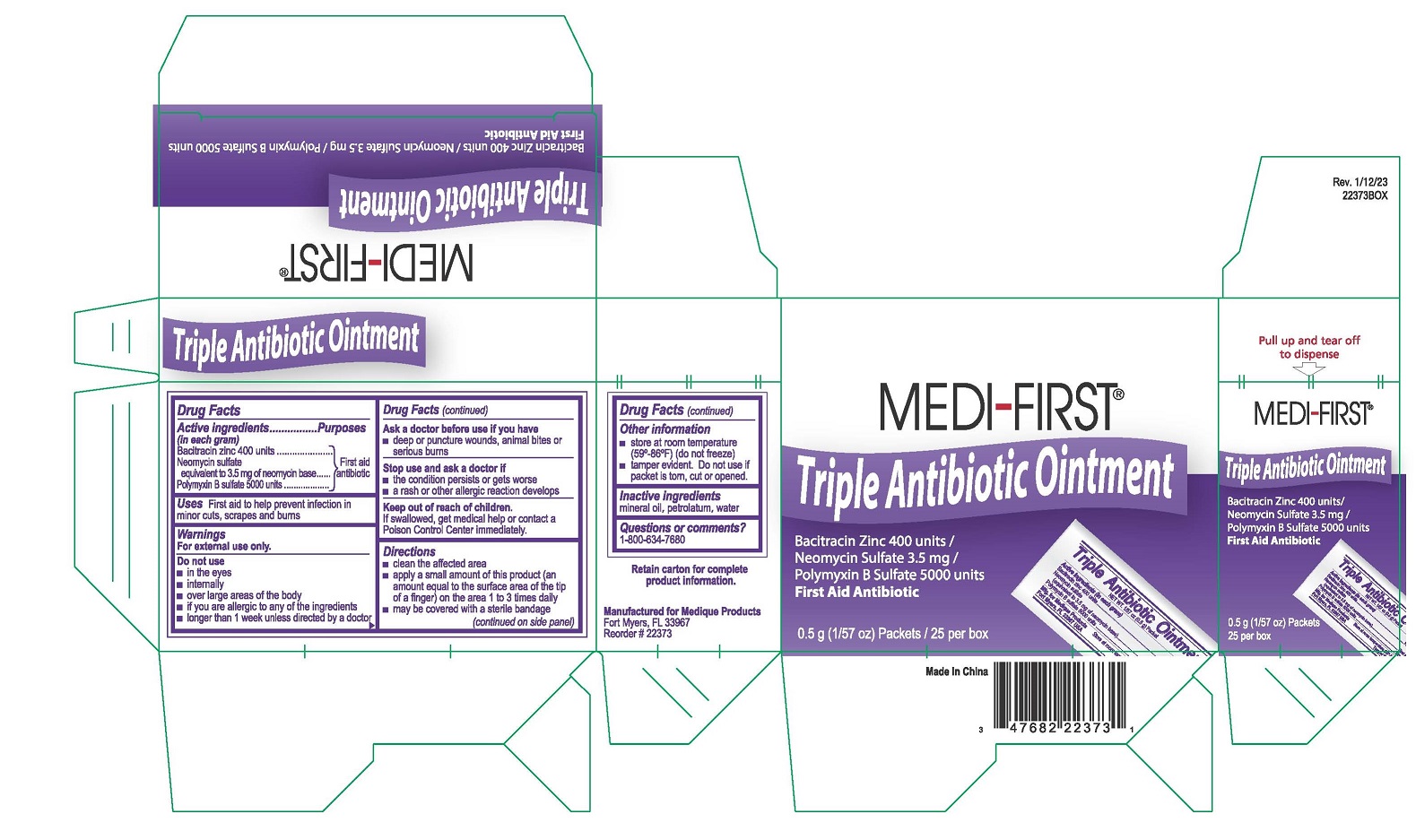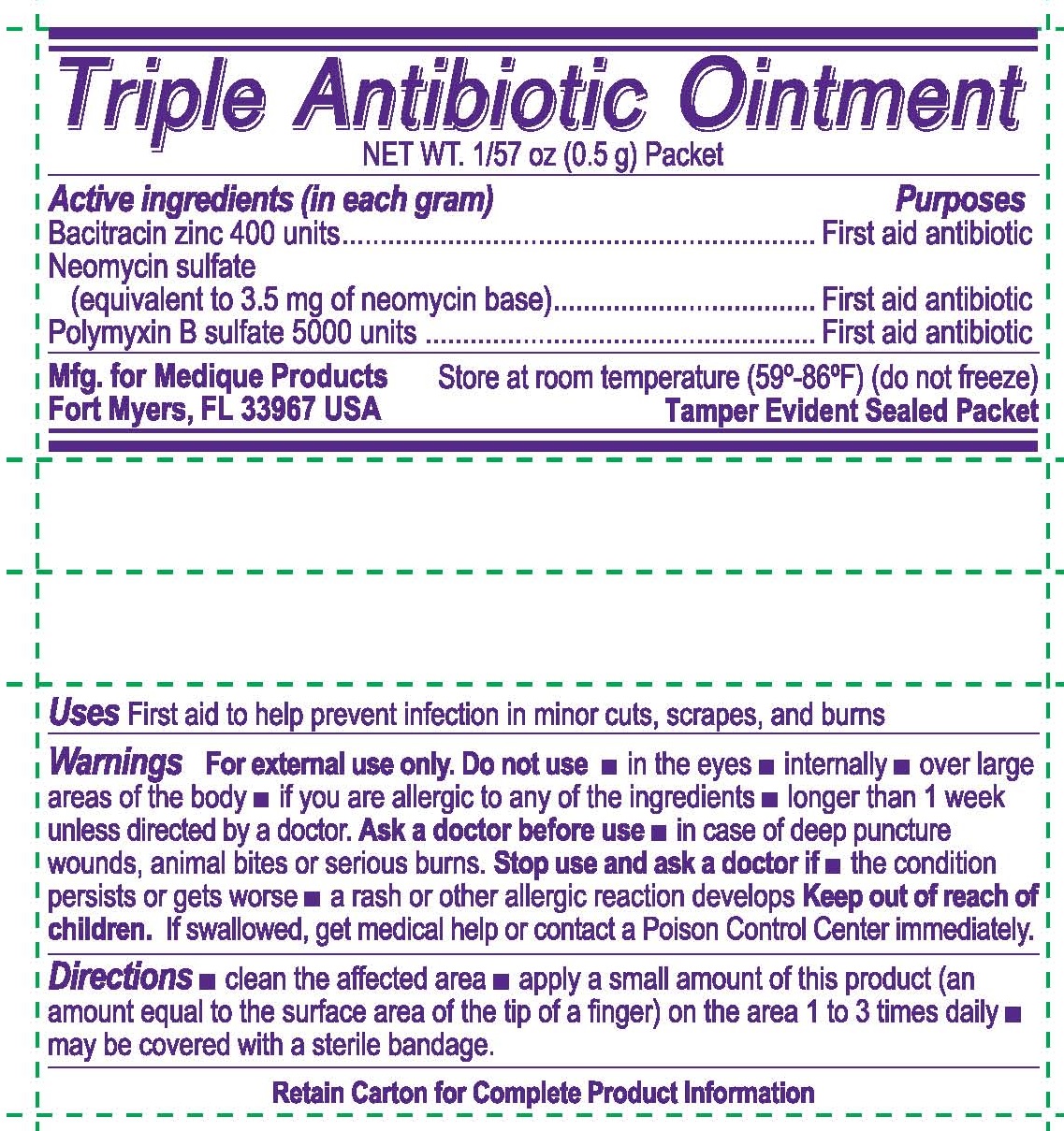 DRUG LABEL: MEDI-FIRST
NDC: 71927-017 | Form: OINTMENT
Manufacturer: Orazen Inc
Category: otc | Type: HUMAN OTC DRUG LABEL
Date: 20250903

ACTIVE INGREDIENTS: BACITRACIN ZINC 400 [USP'U]/1 g; NEOMYCIN SULFATE 0.0035 g/1 g; POLYMYXIN B SULFATE 5000 [USP'U]/1 g
INACTIVE INGREDIENTS: MINERAL OIL; PETROLATUM; WATER

71927-017-01, -02, MEDI-FIRST Triple Antibiotic Ointment

Active ingredients

(in each gram)

Bacitracin zinc 400 units

Neoycin sulfate equivalent to 3.5 mg of neomycin base

Polymyxin B sulfate 5,000 units

Purpose

First Aid antibiotic

First Aid antibiotic

First Aid antibiotic

Uses

First aid to help prevent infection in minor cuts, scrapes, and burns

Warning

For external use only.

Do not use

- in the eyes
- internally
- over large areas of the body
- if you are allergic to any of the ingredients
- longer than 1 week unless directed by a doctor

Ask a doctor before use

- in case of deep puncture wounds, animal bites or serious burns.

Stop use and ask a doctor if

- the condition persists or gets worse
- a rash or other allergic reaction develops

Keep out of reach of children.

If swallowed, get medical help or contact a Poison Control Center immediately.

Directions

- clean the affected area
- apply a small amount of this product (an amount equal to the surface area of the tip of a finger) on the area 1 to 3 times daily
- may be covered with a sterile bandage

Other information

- store at room temperature (59°-86°F) (do not freeze)
- tamper evident. Do not use if packet is torn, cut or opened.

Inactive ingredients

mineral oil, petrolatum, water

Questions or comments?

1-800-634-7680